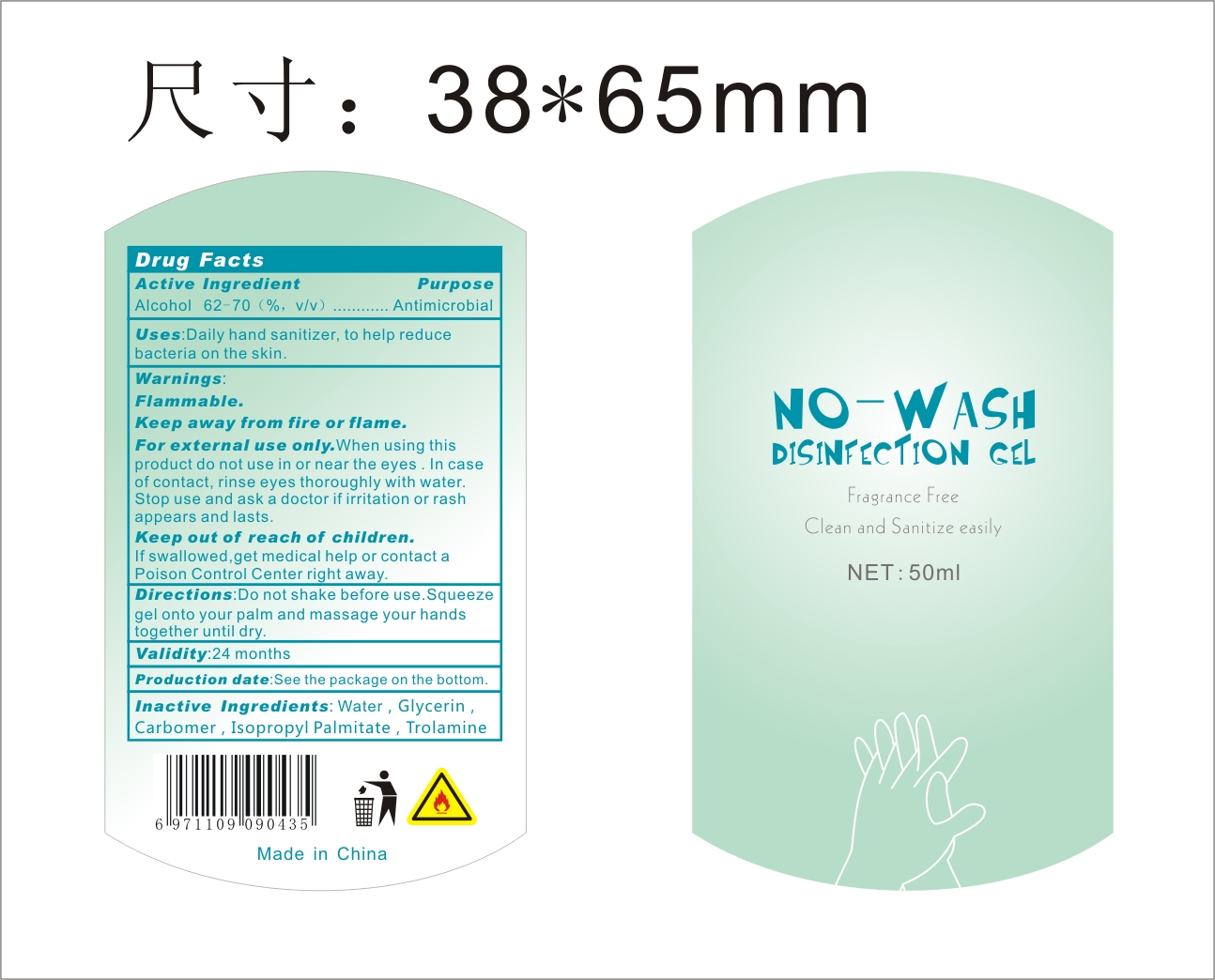 DRUG LABEL: Hand sanitizer
NDC: 76635-003 | Form: GEL
Manufacturer: Hangzhou Glamcos Biotech CO.,LTD
Category: otc | Type: HUMAN OTC DRUG LABEL
Date: 20231123

ACTIVE INGREDIENTS: ALCOHOL 66 mL/100 mL
INACTIVE INGREDIENTS: CARBOMER INTERPOLYMER TYPE A (ALLYL SUCROSE CROSSLINKED); ISOPROPYL PALMITATE; GLYCERIN; TROLAMINE; WATER

Active Ingredient(s)

Alcohol 62-70%(v/v)

Purpose

Antimicrobial

Use

Daily hand sanitizer, to help reduce bacteria on the skin.

Warnings

Flammable.Keep away fire or flame.
For external use only.When using this product do not use in or near the eyes.In case of contact,rinse eyes thotoughly with water.Stop use and ask a doctor of irriration or rash appears and lasts.

Keep out of reach of children.If swallowed,get medical help or contact a poison control center right away.

Directions

Do not shake before use.Squeeze gel onto your palm and massage your hands together until dry.

Other information

Validity:24 months

Production date:See the package in the bottom.

Inactive ingredients

Water，Glycerin，Carbomer，Isopropyl Palmitate，Trolamine